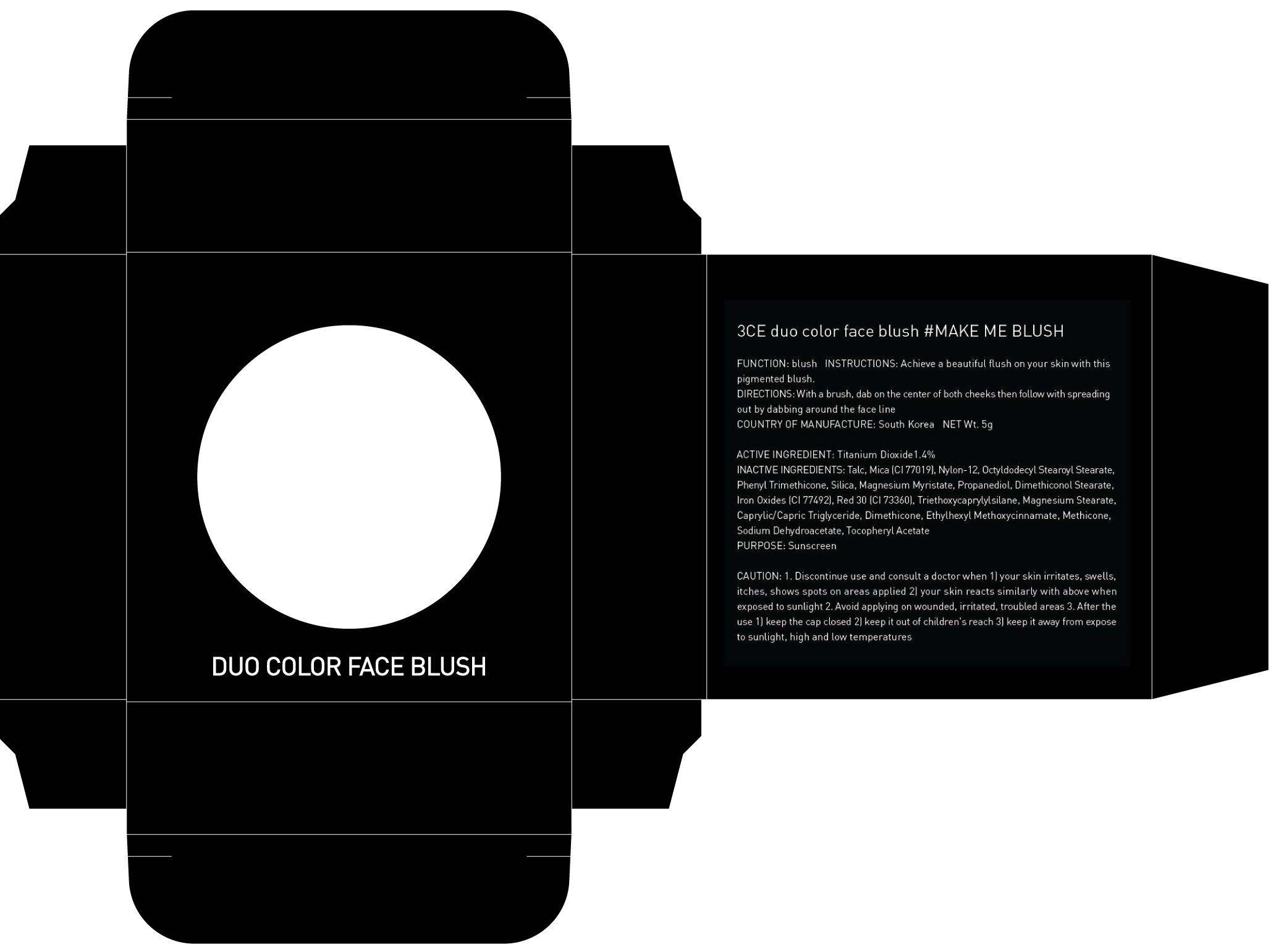 DRUG LABEL: 3CE DUO COLOR FACE BLUSH MAKE ME BLUSH
NDC: 60764-058 | Form: POWDER
Manufacturer: Nanda Co., Ltd
Category: otc | Type: HUMAN OTC DRUG LABEL
Date: 20161004

ACTIVE INGREDIENTS: Titanium Dioxide 0.07 g/5 g
INACTIVE INGREDIENTS: Talc; Mica

ACTIVE INGREDIENT

Active Ingredient: Titanium Dioxide 1.4%

INACTIVE INGREDIENT

Inactive Ingredients: Talc, Mica (CI 77019), Nylon-12, Octyldodecyl Stearoyl Stearate, Phenyl Trimethicone, Silica, Magnesium Myristate, Propanediol, Dimethiconol Stearate, Iron Oxides (CI 77492), Red 30 (CI 73360), Triethoxycaprylylsilane, Magnesium Stearate, Caprylic/Capric Triglyceride, Dimethicone, Ethylhexyl Methoxycinnamate, Methicone, Sodium Dehydroacetate, Tocopheryl Acetate

PURPOSE

Purpose: Sunscreen

CAUTION

CAUTION: 1. Discontinue use and consult a doctor when - your skin irritates, swells, itches, shows spots on areas applied - your skin reacts similarly with above when exposed to sunlight 2. Avoid applying on wounded, irritated, troubled areas 3. After the use - keep the cap closed - keep it out of children's reach - keep it away from expose to sunlight, high and low temperatures

DESCRIPTION

INSTRUCTIONS: Achieve a beautiful flush on your skin with this pigmented blush.

Directions: With a brush, dab on the center of both cheeks then follow with spreading out by dabbing around the face line